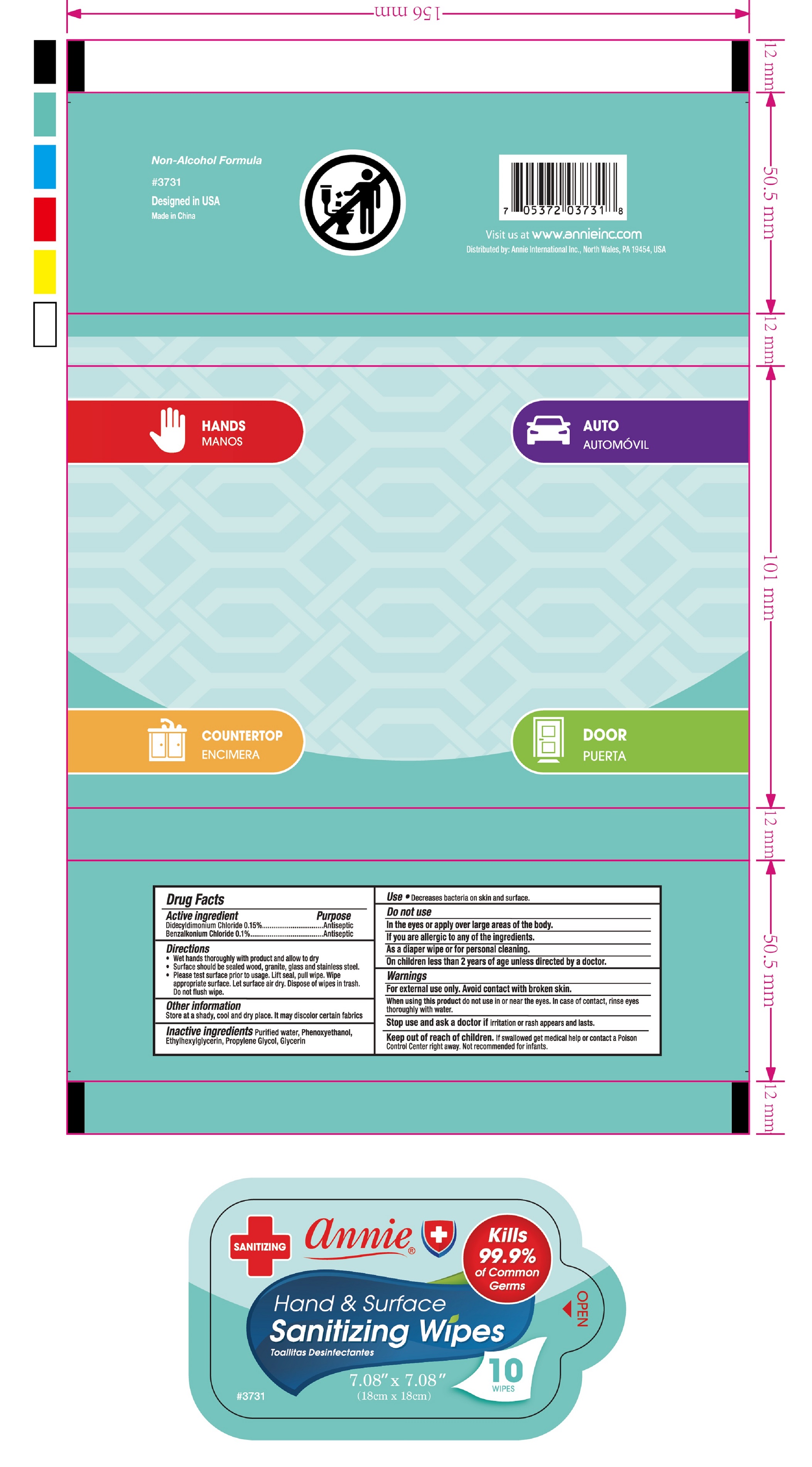 DRUG LABEL: Sanitizing Wipes
NDC: 75629-010 | Form: CLOTH
Manufacturer: ANNIE INTERNATIONAL, INC
Category: otc | Type: HUMAN OTC DRUG LABEL
Date: 20200907

ACTIVE INGREDIENTS: BENZALKONIUM CHLORIDE 0.1 g/100 1; DIDECYLDIMONIUM CHLORIDE 0.15 g/100 1
INACTIVE INGREDIENTS: GLYCERIN; PROPYLENE GLYCOL; WATER; ETHYLHEXYLGLYCERIN; PHENOXYETHANOL

75629-010-01 Sanitizing Wipes Ningbo Chenxing Daily Necessities Co., Ltd.

Active Ingredient(s)

Didecyldimonium Chloride 0.15%,Benzalkonium Chloride 0.1%. Purpose: Antiseptic

Purpose

Antiseptic, Sanitizing Wipes

Directions

- Wet hands thoroughly with product and allow to dry
- Surface should be sealed wood, granite, glass and stainless steel.
- Please test surface prior to usage. Lift seal, pull wipe. Wipe appropriate surface. Let surface air dry. Dispose of wipes in trash. Do not flush wipe.

Other information

Store at a shady, cool and dry place. It may discolor certain fabrics.

Inactive ingredients

Purified Water, Phenoxyethanol, Ethylhexylglycerin, Propylene Glycol, Glycerin.

Use

Decreases bacteria on skin and surface.

Do not use

- In the eyes or apply over large areas of the body.
- If you are allergic to any of the ingredients.
- As a diaper wipe or for personal cleaning.
- On children less than 2 years of age unless directed by a doctor.

Warnings

- Fof external use only. Avoid contact with broken skin.
  - When using this product do not use in near the eyes. In case of contact, rinse eyes thoroughly with water.

When using this product do not use in near the eyes. In case of contact, rinse eyes thoroughly with water.

Stop use and ask a doctor if irritation or rash appears and lasts.

Keep out of reach of children. If swallowed get medical help or contact a Poison Control Center right away. Not recommended for infants.

Package Label - Principal Display Panel

10 Wipes NDC:75629-010-01